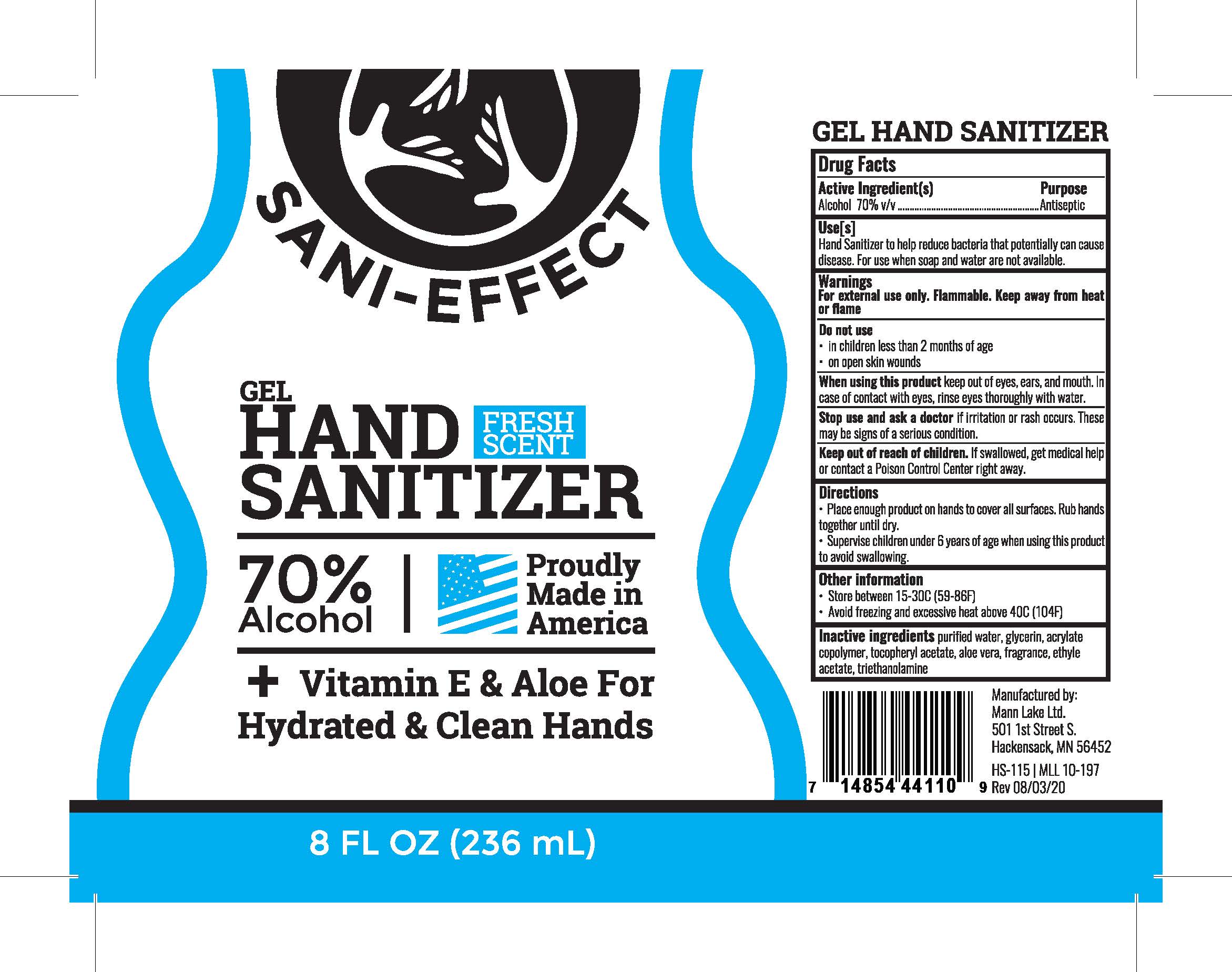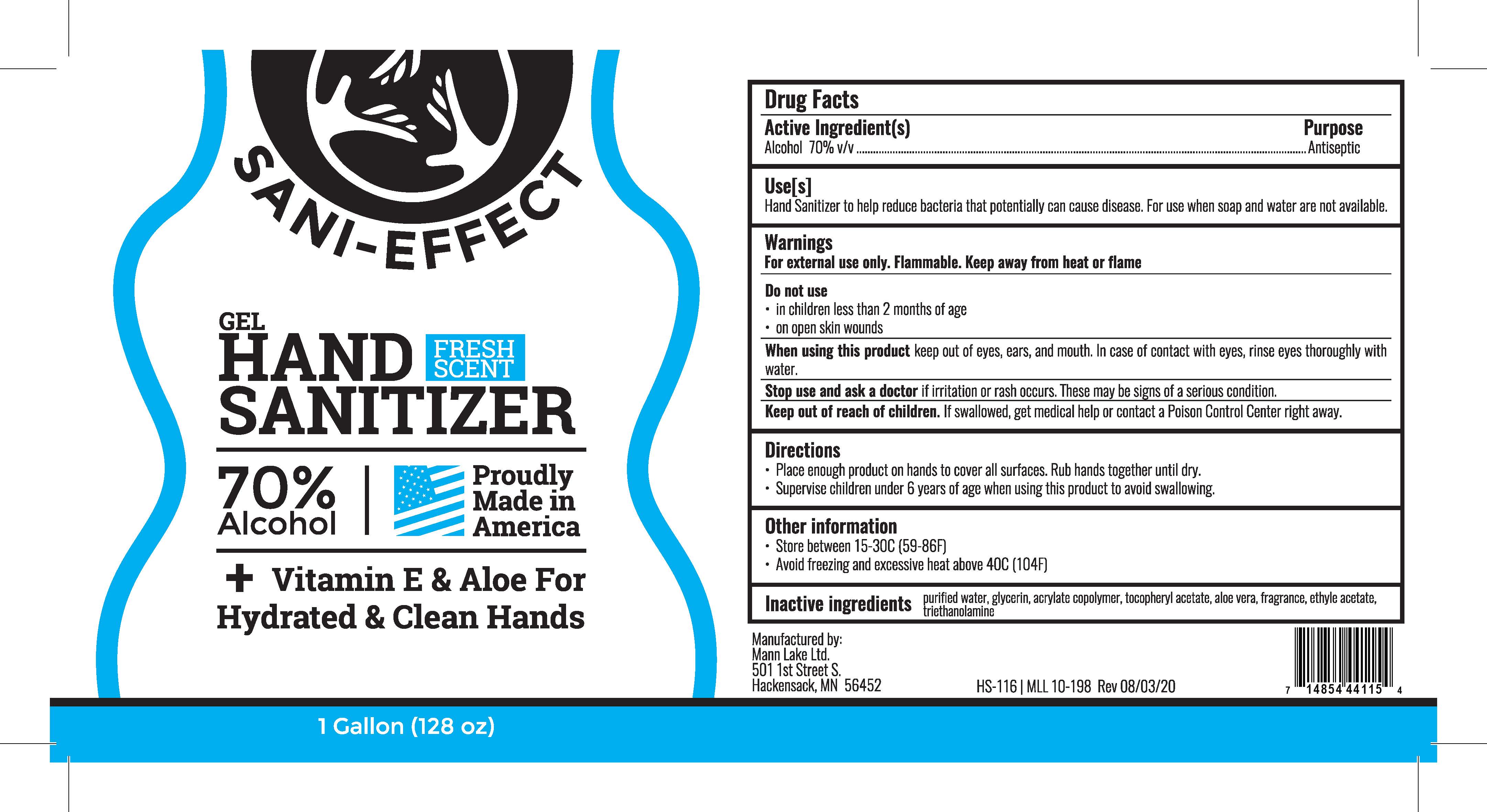 DRUG LABEL: SDA 40B
NDC: 80194-0116 | Form: SOLUTION
Manufacturer: Mann Lake Ltd
Category: otc | Type: HUMAN OTC DRUG LABEL
Date: 20220829

ACTIVE INGREDIENTS: ALCOHOL 70 L/100 L
INACTIVE INGREDIENTS: WATER 30 L/100 L

Sani-Effect Gel Hand sanitizer Fresh Scent with Viatmin E and Aloe Vera

This is a hand sanitizer.

Active Ingredient(s)

Alcohol 70% v/v. Purpose Antiseptic

Purpose

Antiseptic, Hand Sanitizer

Use

Hand sanitizer to help reduce bacteria that can potentially cause disease. For use when soap and water are not available.

Warnings

For external use only. Flammable. Keep away from heat or flame.

Di not use

- in children less than 2 months of age
- on open skin wounds

When using this product keep out of eyes, ears, and mouth. In case of contact with eyes, rinse eyes thoroughly with water.

Stop use and ask a doctor if irritation or rash occurs. These may be signs of a serious condition.

Keep out of reach of children. If swallowed, get medical help or contact a Poison Control Center right away.

Stop use and ask a doctor if irriatation or rash occurs. These may be signs of a serious condition.

Keep out of reach of children. If swallowed, get medical help or contact a Poison Control center right away.

Directions

- Place enough product on the hands to cover all surfaces. Rub hands together until dry.
- Supervise children under 6 years of age when using this product to avoid swallowing.

Other Information

- Store between 15-30C (59-86F)
- Avoid freezing and excessive heat above 40C (104F)

Inactive Ingredients

glycerin, triethanolamine, carbomer, ethyl acetate, vitamin E, aloe vera, fragrance, purified water USP